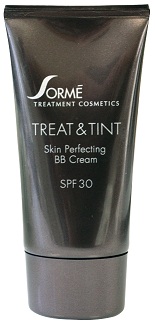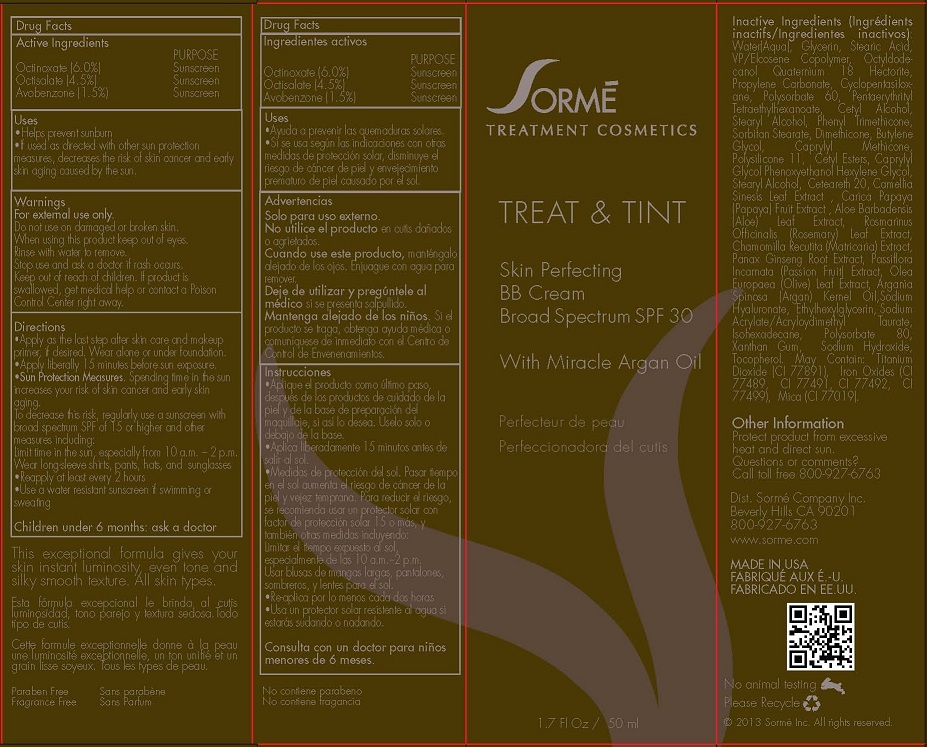 DRUG LABEL: TREAT AND TINT SKIN PERFECTING BB
NDC: 54754-101 | Form: CREAM
Manufacturer: SORME COMPANY INC
Category: otc | Type: HUMAN OTC DRUG LABEL
Date: 20130106

ACTIVE INGREDIENTS: OCTINOXATE 6 g/100 mL; OCTISALATE 4.5 g/100 mL; AVOBENZONE 1.5 g/100 mL
INACTIVE INGREDIENTS: WATER; GLYCERIN; STEARIC ACID; PVP/VA COPOLYMER; OCTYLDECANOL; QUATERNIUM-18; HECTORITE; PROPYLENE CARBONATE; CYCLOMETHICONE 5; POLYSORBATE 60; PENTAERYTHRITYL TETRAETHYLHEXANOATE; CETYL ALCOHOL; STEARYL ALCOHOL; PHENYL TRIMETHICONE; SORBITAN MONOSTEARATE; DIMETHICONE; BUTYLENE GLYCOL; CAPRYLYL TRISILOXANE; POLYSILICONE-15; CETYL ESTERS WAX; CAPRYLYL GLYCOL; PHENOXYETHANOL; HEXYLENE GLYCOL; CETEARETH-22; CAMELLIA SINENSIS WHOLE; CARICA PAPAYA WHOLE; ALOE VERA LEAF; ROSMARINUS OFFICINALIS WHOLE; MATRICARIA CHAMOMILLA WHOLE; PANAX GINSENG ROOT WATER; PASSIFLORA INCARNATA FRUIT; OLEA EUROPAEA LEAF; ARGAN OIL; HYALURONATE SODIUM; ETHYLHEXYLGLYCERIN; SODIUM ACRYLATE/SODIUM ACRYLOYLDIMETHYLTAURATE COPOLYMER (4000000 MW); ISOHEXADECANE; POLYSORBATE 80; XANTHAN GUM; SODIUM HYDROXIDE; TOCOPHEROL; TITANIUM DIOXIDE; BROWN IRON OXIDE; MICA

ACTIVE INGREDIENTS

OCTINOXATE (6.0%)

OCTISALATE (4.5%)

AVOBENZONE (1.5%)

PURPOSE

SUNSCREEN

USES

- HELPS PREVENT SUNBURN
- IF USED AS DIRECTED WITH OTHER SUN PROTECTION MEASURES, DECREASES THE RISK OF SKIN CANCER AND SKIN AGING CAUSED BY THE SUN.

WARNINGS

FOR EXTERNAL USE ONLY.

DO NOT USE ON DAMAGED OR BROKEN SKIN.

WHEN USING THIS PRODUCT KEEP OUT OF EYES.

RINSE WITH WATER TO REMOVE.

STOP USE AND ASK A DOCTOR IF RASH OCCURS.

KEEP OUT OF REACH OF CHILDREN. IF PRODUCT IS SWALLOWED, GET MEDICAL HELP OR CONTACT A POISON CONTROL CENTER RIGHT AWAY.

DIRECTIONS

- APPLY AS THE LAST STEP AFTER SKIN CARE AND MAKEUP PRIMER, IF DESIRED. WEAR ALONE OR UNDER FOUNDATION.
- APPLY LIBERALLY 15 MINUTES BEFORE SUN EXPOSURE.
- SUN PROTECTION MEASURES. SPENDING TIME IN THE SUN INCREASES YOUR RISK OF SKIN CANCER AND EARLY SKIN AGING. TO DECREASE THIS RISK, REGULARLY USE A SUNSCREEN WITH BROAD SPECTRUM SPF OF 15 OR HIGHER AND OTHER MEASURES INCLUDING:
- LIMIT TIME IN THE SUN, ESPECIALLY FROM 10 A.M. - 2 P.M. WEAR LONG-SLEEVED SHIRTS, PANTS, HATS, AND SUNGLASSES.
- REAPPLY AT LEAST EVERY 2 HOURS.
- USE A WATER RESISTANT SUNSCREEN IF SWIMMING OR SWEATING.

PEDIATRIC USE

CHILDREN UNDER 6 MONTHS: ASK A DOCTOR.

INACTIVE INGREDIENTS

WATER, GLYCERIN, STEARIC ACID, VP/EICOSENE COPOLYMER, OCTYLDODECANOL, QUATERNIUM 18, HECTORITE, PROPYLENE CARBONATE, CYCLOPENTASILOXANE, POLYSORBATE 60, PENTAERYTHRITYL TETRAETHYLHEXANOATE, CETYL ALCOHOL, STEARYL ALCOHOL, PHENYL TRIMETHICONE, SORBITAN STEARATE, DIMETHICONE, BUTYLENE GLYCOL, CAPRYLYL METHICONE, POLYSILICONE 11, CETYL ESTERS, CAPRYLYL GLYCOL, PHENOXYETHANOL, HEXYLENE GLYCOL, STEARYL ALCOHOL, CETEARETH 20, CAMELLIA SINESIS LEAF EXTRACT, CARICA PAPAYA (PAPAYA) FRUIT EXTRACT, ALOE BARBADENSIS (ALOE) LEAF EXTRACT, ROSMARINUS OFFICINALIS (ROSEMARY) LEAF EXTRACT, CHAMOMILLA RECUTITA (MATRICARIA) EXTRACT, PANAX GINSENG ROOT EXTRACT, PASSIFLORA INCARNATA (PASSION FRUIT) EXTRACT, OLEA EUROPAEA (OLIVE) LEAF EXTRACT, ARGANIA SPINOSA (ARGAN) KERNEL OIL, SODIUM HYALURONATE, ETHYLHEXYLGLYCERIN, SODIUM ACRYLATE/ACRYLOYDIMETHYL TAURATE, ISOHEXADECANE, POLYSORBATE 80, XANTHAN GUM, SODIUM HYDROXIDE, TOCOPHEROL. MAY CONTAIN: TITANIUM DIOXIDE (CI 77891), IRON OXIDES (CI 77489, CI 77491, CI 77492, CI 77499), MICA (CI 77019).

OTHER INFORMATION

PROTECT PRODUCT FROM EXCESSIVE HEAT AND DIRECT SUN.

QUESTIONS OR COMMENTS?

CALL TOLL FREE 800-927-6763